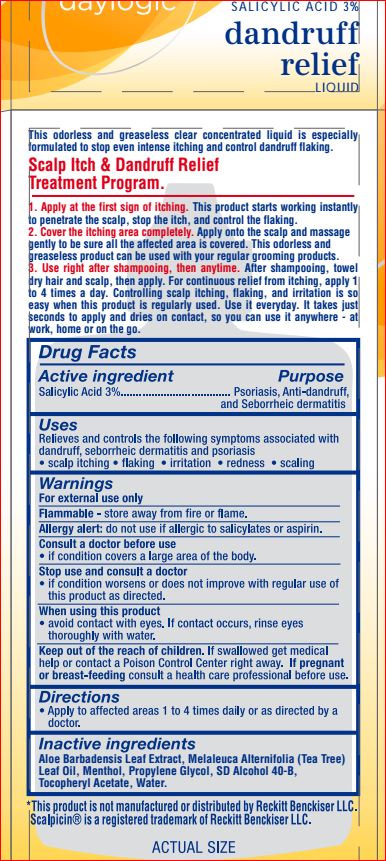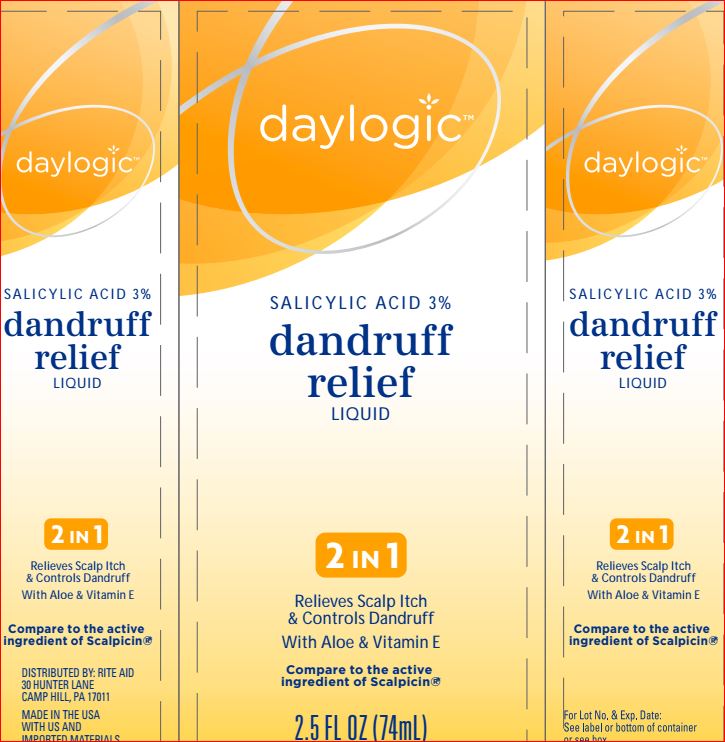 DRUG LABEL: Dandruff Relief
NDC: 11822-1237 | Form: LIQUID
Manufacturer: Rite Aid
Category: otc | Type: HUMAN OTC DRUG LABEL
Date: 20180621

ACTIVE INGREDIENTS: Salicylic Acid 3 g/100 mL
INACTIVE INGREDIENTS: ALOE VERA LEAF; TEA TREE OIL; Menthol; Propylene Glycol; ALCOHOL; .ALPHA.-TOCOPHEROL ACETATE; Water

Drug Facts

Active ingredient Purpose
Salicylic Acid 3%.................................... Psoriasis, Anti-dandruff,
and Seborrheic dermatitis

Uses
Relieves and controls the following symptoms associated with
dandruff, seborrheic dermatitis and psoriasis
• scalp itching • flaking • irritation • redness • scaling

Warnings
For external use only
Flammable - store away from fire or flame.
Allergy alert: do not use if allergic to salicylates or aspirin.
Consult a doctor before use
• if condition covers a large area of the body.
Stop use and consult a doctor
• if condition worsens or does not improve with regular use of
this product as directed.
When using this product
• avoid contact with eyes. If contact occurs, rinse eyes
thoroughly with water.
Keep out of the reach of children. If swallowed get medical
help or contact a Poison Control Center right away. If pregnant
or breast-feeding consult a health care professional before use.

Directions
• Apply to affected areas 1 to 4 times daily or as directed by a doctor.

Inactive ingredients
Aloe Barbadensis Leaf Extract, Melaleuca Alternifolia (Tea Tree)
Leaf Oil, Menthol, Propylene Glycol, SD Alcohol 40-B,
Tocopheryl Acetate, Water.